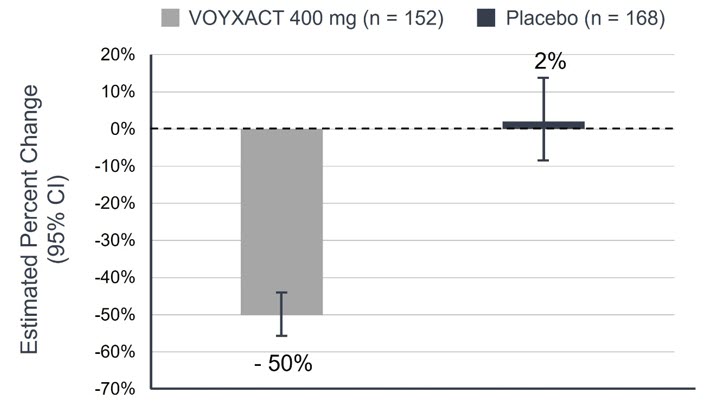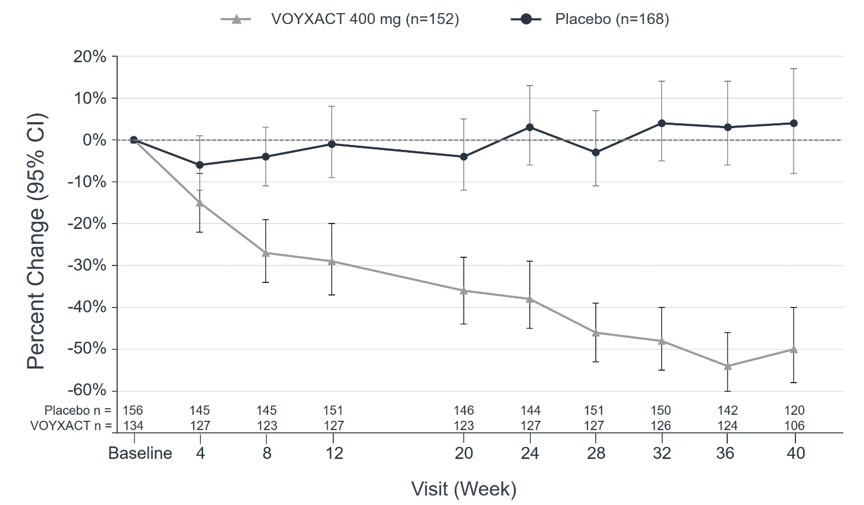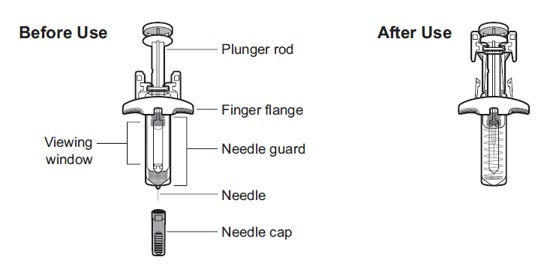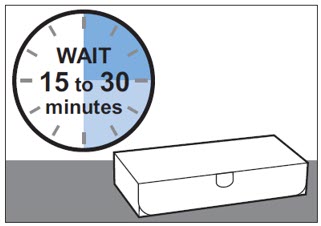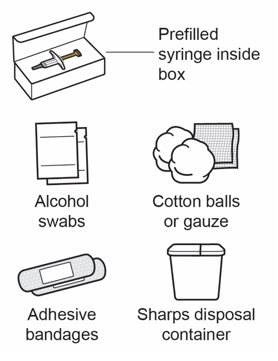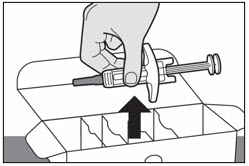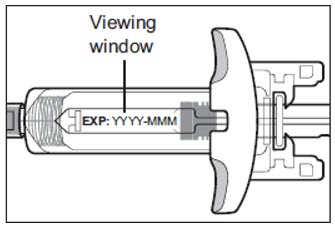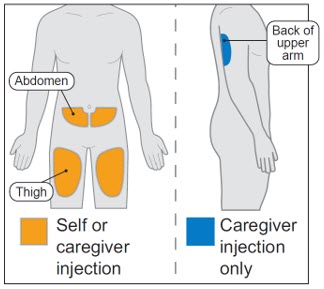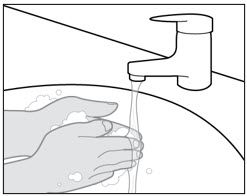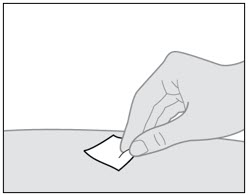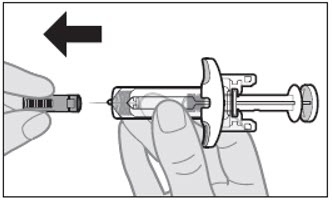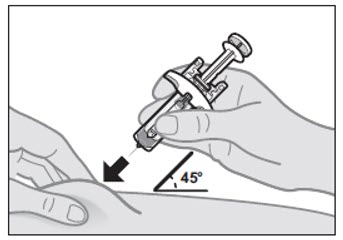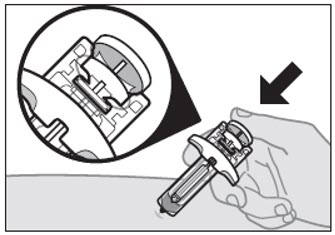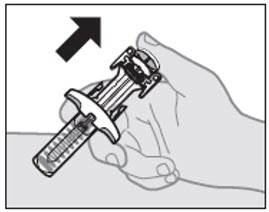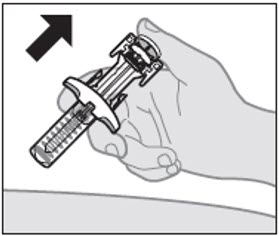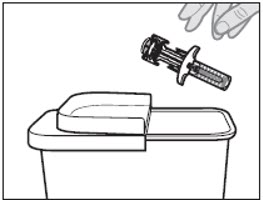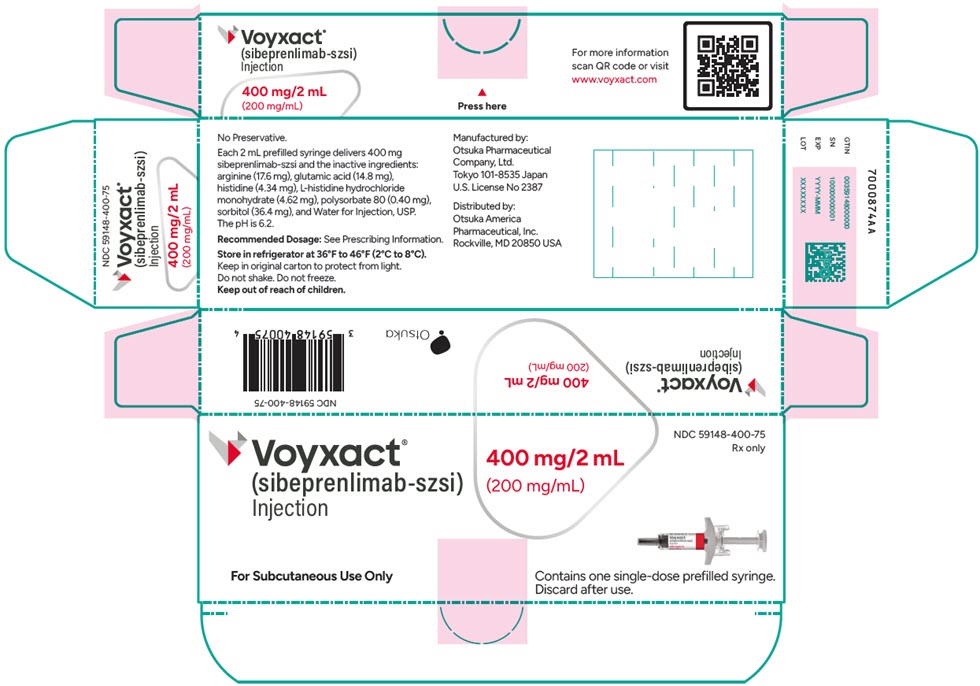 DRUG LABEL: VOYXACT
NDC: 59148-400 | Form: INJECTION
Manufacturer: Otsuka America Pharmaceutical, Inc.
Category: prescription | Type: HUMAN PRESCRIPTION DRUG LABEL
Date: 20251130

ACTIVE INGREDIENTS: sibeprenlimab 200 mg/1 mL
INACTIVE INGREDIENTS: arginine; glutamic acid; histidine; polysorbate 80; sorbitol; WATER

HIGHLIGHTS OF PRESCRIBING INFORMATION

These highlights do not include all the information needed to use VOYXACT safely and effectively. See full prescribing information for VOYXACT.
VOYXACT® (sibeprenlimab-szsi) injection, for subcutaneous use
Initial U.S. Approval: 2025

1 INDICATIONS AND USAGE

VOYXACT is an A Proliferation Inducing Ligand (APRIL) blocker, indicated to reduce proteinuria in adults with primary immunoglobulin A nephropathy (IgAN) at risk for disease progression. (1)

This indication is approved under accelerated approval based on reduction of proteinuria. It has not been established whether VOYXACT slows kidney function decline over the long-term in patients with IgAN. Continued approval for this indication may be contingent upon verification and description of clinical benefit in a confirmatory clinical trial. (1)

2 DOSAGE AND ADMINISTRATION

Recommended dosage: 400 mg injected subcutaneously once every 4 weeks. (2.1)

3 DOSAGE FORMS AND STRENGTHS

Injection: 400 mg/2 mL (200 mg/mL) in a single-dose prefilled syringe. (3)

4 CONTRAINDICATIONS

Serious hypersensitivity to sibeprenlimab-szsi or any excipients in VOYXACT. (4)

5 WARNINGS AND PRECAUTIONS

- Immunosuppression and Increased Risk of Infections: Before initiating VOYXACT, assess for active infections. During treatment, monitor for signs and symptoms of infection. (5.1)
- Immunosuppression and Immunization Risks: Live vaccines not recommended within 30 days prior to initiation of VOYXACT or during treatment. (5.2)

6 ADVERSE REACTIONS

Most common adverse reactions are upper respiratory tract infection and injection site erythema. (6.1)

To report SUSPECTED ADVERSE REACTIONS, contact Otsuka America Pharmaceutical, Inc. at 1-800-438-9927 or FDA at 1-800-FDA-1088 or www.fda.gov/medwatch.

FULL PRESCRIBING INFORMATION

1 INDICATIONS AND USAGE

VOYXACT is indicated to reduce proteinuria in adults with primary immunoglobulin A nephropathy (IgAN) at risk for disease progression.

This indication is approved under accelerated approval based on reduction of proteinuria. It has not been established whether VOYXACT slows kidney function decline over the long-term in patients with IgAN. Continued approval for this indication may be contingent upon verification and description of clinical benefit in a confirmatory clinical trial.

2 DOSAGE AND ADMINISTRATION

2.1 Recommended Dosage

The recommended dosage of VOYXACT is 400 mg administered by subcutaneous injection once every 4 weeks.

2.2 Missed Dose

If a scheduled dose of VOYXACT is missed, administer the missed dose as soon as possible and then resume dosing every 4 weeks thereafter.

2.3 Preparation and Administration

VOYXACT is intended for patient self-administration or for administration by a caregiver. Provide proper training to patients and/or caregivers on the administration of VOYXACT prior to use according to the "Instructions for Use".

Visually inspect the prefilled syringe for particulate matter and discoloration. The solution should be clear to opalescent and colorless to yellow. Do not use the prefilled syringe if the solution contains visible particulate matter, is cloudy or discolored (other than clear to opalescent, colorless to yellow).

Allow VOYXACT prefilled syringe to come to room temperature up to 77°F (25°C) for 15 to 30 minutes before giving an injection. Keep VOYXACT prefilled syringe in the original carton to protect it from light. Once VOYXACT prefilled syringe has reached room temperature, do not return it to the refrigerator. Do not use VOYXACT if it has been at room temperature for 7 days or longer.

Administer VOYXACT by subcutaneous injection only. Inject into the front of the thigh or abdomen. The back of the upper arm can also be used as an injection site if administered subcutaneously by a caregiver. Do not inject into the same site used for the previous injection, or into moles, scars, bruises or areas where the skin is tender, damaged, red, scaly, or hard.

3 DOSAGE FORMS AND STRENGTHS

Injection: 400 mg/2 mL (200 mg/mL) clear to opalescent, colorless to yellow, solution in a single-dose prefilled syringe.

4 CONTRAINDICATIONS

VOYXACT is contraindicated in patients with serious hypersensitivity to sibeprenlimab-szsi or any of the excipients of VOYXACT.

5 WARNINGS AND PRECAUTIONS

5.1 Immunosuppression and Increased Risk of Infections

VOYXACT suppresses the immune system by reducing antibody production, which may increase the risk of infections. Patients with chronic or recurring infections may have an increased risk of serious infection. In clinical trials, infections occurred in 49% of patients treated with VOYXACT compared with 45% of patients treated with placebo.

Before initiating VOYXACT, assess patients for active infections. During treatment, monitor patients for signs and symptoms of infection. If a serious infection develops, consider interrupting VOYXACT until the infection is controlled.

There are limited clinical study data with concomitant use of VOYXACT and systemic immuno-suppressants. Consider the potential for increased immunosuppression when coadministering VOYXACT and immuno-suppressants or when initiating VOYXACT before or after immuno-suppressive therapy.

5.2 Immunosuppression and Immunization Risks

Because of its mechanism of action, VOYXACT may interfere with the immune responses to vaccines and increase the risk of infection from live vaccines. Live vaccines are not recommended within 30 days prior to initiation of VOYXACT or during treatment with VOYXACT as safety has not been established. No data are available on the secondary transmission of infection from persons receiving live vaccines to patients receiving VOYXACT or on the efficacy of immunizations administered while receiving VOYXACT.

6 ADVERSE REACTIONS

The following clinically significant adverse reactions are described elsewhere in the labeling:

- Immunosuppression and Increased Risk of Infections [see Warnings and Precautions (5.1)]
- Immunosuppression and Immunization Risks [see Warnings and Precautions (5.2)]

6.1 Clinical Trials Experience

Because clinical trials are conducted under widely varying conditions, adverse reaction rates observed in the clinical trials of a drug cannot be directly compared to rates in the clinical trials of another drug and may not reflect the rates observed in practice.

The safety of VOYXACT was evaluated in a randomized, double-blind, placebo-controlled, clinical study in patients with IgAN (VISIONARY). The median duration of exposure was 44 weeks in the 259 patients treated with VOYXACT and 48 weeks in the 251 patients administered placebo. The most common adverse reactions (reported in ≥10% of patients treated with VOYXACT and at a higher incidence than placebo) in patients treated with VOYXACT and placebo, respectively, were infections (49% versus 45%) and injection site reactions (24% versus 23%). The most common infection was upper respiratory infection (15% versus 14%), and the most common injection site reaction was injection site erythema (13% versus 12%). Most adverse reactions were reported as mild or moderate in severity and resolved without treatment interruption or discontinuation.

8 USE IN SPECIFIC POPULATIONS

8.1 Pregnancy

Risk Summary

There are no available data on VOYXACT use in pregnant women to evaluate for a drug-associated risk of major birth defects, miscarriage or other adverse maternal or fetal outcomes. Monoclonal antibodies, such as sibeprenlimab-szsi, can be actively transported across the placenta as pregnancy progresses; therefore, potential effects on a fetus are likely to be greater during the second and third trimester of pregnancy (see Clinical Considerations). In an enhanced prenatal and postnatal development (ePPND) toxicity study, administration of sibeprenlimab-szsi subcutaneously to pregnant monkeys did not result in any adverse effects on embryofetal or postnatal development at exposures approximately 10-times the clinical exposure at the maximum recommended human dose (MRHD) based on area under the curve (AUC) (see Data).

The background risk of major birth defects and miscarriage for the indicated population are unknown. All pregnancies have a background risk of birth defect, loss or other adverse outcomes. In the U.S. general population, the estimated background risk of major birth defects and miscarriage in clinically recognized pregnancies is 2% to 4% and 15% to 20%, respectively.

Pregnant women exposed to VOYXACT, or their healthcare providers, should report VOYXACT exposure by calling 1-833-869-9228 or visiting www.VOYXACT.com.

Clinical Considerations

Disease-Associated Maternal and/or Embryo/Fetal Risk

IgA nephropathy is associated with adverse maternal outcomes, including increased rates of cesarean section, pregnancy-induced hypertension, pre-eclampsia and preterm delivery, and adverse fetal/neonatal outcomes, including stillbirth and low birth weight.

Fetal/Neonatal Adverse Reactions

Transport of endogenous IgG antibodies across the placenta increases as pregnancy progresses, and peaks during the third trimester. Therefore, VOYXACT may be present in infants exposed in utero. Consider the potential clinical impact of VOYXACT exposure in infants who were exposed to VOYXACT in utero.

Data

Animal Data

In an ePPND toxicity study, subcutaneous administration of sibeprenlimab-szsi once every two weeks to pregnant cynomolgus monkeys from gestation Day 20 through delivery (includes the period of organogenesis) did not result in any adverse effect on embryofetal or postnatal development at the single tested dose of 101 mg/kg, which provided an approximately 10-fold margin to the clinical exposure at the MRHD based on AUC.

8.2 Lactation

Risk Summary

There are no data on the presence of sibeprenlimab-szsi in human milk, the effects of sibeprenlimab-szsi on the breastfed infant, or the effects of sibeprenlimab-szsi on milk production. Endogenous maternal IgG and monoclonal antibodies are transferred into human milk. The effects of local gastrointestinal exposure on sibeprenlimab-szsi in the breastfed infant are unknown. The developmental and health benefits of breastfeeding should be considered along with the mother's clinical need for VOYXACT and any potential adverse effects on the breastfed child from VOYXACT or from the underlying maternal condition.

8.4 Pediatric Use

Safety and effectiveness of VOYXACT in pediatric patients have not been established.

8.5 Geriatric Use

Clinical studies of VOYXACT did not include sufficient numbers of patients aged 65 and over to determine whether they respond differently from younger adult patients.

No clinically meaningful differences in the pharmacokinetics of VOYXACT were observed in patients aged 65 and over compared to younger adult patients [see Clinical Pharmacology (12.3)].

11 DESCRIPTION

VOYXACT contains sibeprenlimab-szsi, an A Proliferation Inducing Ligand (APRIL) blocker and humanized immunoglobulin G2 (IgG2) monoclonal antibody produced by Chinese Hamster Ovary (CHO) cells.

The approximate molecular weight of sibeprenlimab-szsi is 146 kDa.

VOYXACT (sibeprenlimab-szsi) injection is a sterile, preservative-free, clear to opalescent, colorless to yellow solution in a single-dose prefilled syringe for subcutaneous use.

Each 2 mL prefilled syringe delivers 400 mg sibeprenlimab-szsi and the inactive ingredients: arginine (17.6 mg), glutamic acid (14.8 mg), histidine (4.34 mg), L-histidine hydrochloride monohydrate (4.62 mg), polysorbate 80 (0.40 mg), sorbitol (36.4 mg), and Water for Injection, USP. The pH is 6.2.

12 CLINICAL PHARMACOLOGY

12.1 Mechanism of Action

VOYXACT binds to APRIL with a dissociation constant (KD) of 0.95 pM, which blocks signaling at the B cell maturation antigen (BCMA) and transmembrane activator and calcium modulator and cyclophilin ligand interactor (TACI) receptors. Inhibition of APRIL results in reduced levels of serum galactose-deficient immunoglobulin A1 (Gd-IgA1), which is implicated in the pathogenesis of IgAN.

12.2 Pharmacodynamics

In healthy subjects administered a single 400 mg subcutaneous VOYXACT dose, serum levels of APRIL were reduced by >90% by Day 3 and the reduction was maintained until Day 42.

In IgAN patients treated with VOYXACT every four weeks in the VISIONARY Study, APRIL suppression > 90% was observed by Week 4 and was sustained throughout treatment. Serum Gd-IgA1, IgA, IgG, and IgM levels decreased within 4 weeks, reached a plateau by Week 24, and by Week 48 mean serum levels were reduced from baseline by 67% for Gd-IgA1, 69% for IgA, 35% for IgG, and 75% for IgM.

12.3 Pharmacokinetics

Following 400 mg doses of VOYXACT administered subcutaneously every 4 weeks to patients with IgAN, steady-state is reached by 20 weeks of dosing.

Absorption

Following a single subcutaneous dose of 400 mg VOYXACT in healthy subjects, the median time to reach peak concentration is 8 days.

The absolute bioavailability of sibeprenlimab-szsi is approximately 92% and there is no difference in relative bioavailability following administration to the abdomen, thigh, or arm.

Distribution

The volume of distribution is 4 L.

Elimination

Following a single 400 mg VOYXACT dose, the mean terminal half-life is 9.3 days. The mean apparent clearance of sibeprenlimab-szsi following 400 mg doses every 4 weeks is 206 mL/day.

Metabolism

As an IgG2 monoclonal antibody, sibeprenlimab-szsi is expected to be degraded by proteolytic enzymes via catabolic pathways in the same manner as endogenous IgG.

Specific Populations

No dedicated studies were conducted to evaluate the effects of renal impairment and hepatic impairment on the pharmacokinetics of sibeprenlimab-szsi.

Population pharmacokinetic analysis did not identify any clinically relevant differences in the pharmacokinetics of sibeprenlimab-szsi based on sex, age, weight, race, and mild to moderate renal impairment (eGFR: 30 to 89 mL/min).

12.6 Immunogenicity

The observed incidence of anti-drug antibodies (ADA) is highly dependent on the sensitivity and specificity of the assay. Differences in assay methods preclude meaningful comparisons of the incidence of ADA in the study described below with the incidence of ADA in other studies, including those of sibeprenlimab-szsi.

During the treatment period in the VISIONARY Study, 88 of 256 (34%) evaluable patients treated with VOYXACT developed ADA. Among the 88 patients who tested positive for ADA, 21 patients (23.9%) developed ADA that had neutralizing activity. Sibeprenlimab-szsi exposure in patients with IgAN who developed ADA was ~ 40% lower than in patients with undetectable ADA over the treatment period. The reduction in urine protein/creatinine ratio based on 24-hour urine collections (uPCR-24h) from baseline to Month 9 was numerically lower in patients who developed ADA (41.6%) compared to those who did not (52.7%). The clinical significance of the differences in uPCR reduction according to the presence or absence of ADA is not clear. The presence of ADA did not have a clinically significant effect on the incidence or severity of adverse reactions.

13 NONCLINICAL TOXICOLOGY

13.1 Carcinogenesis, Mutagenesis, Impairment of Fertility

No carcinogenicity or mutagenicity studies have been conducted with sibeprenlimab-szsi.

Impairment of Fertility

In cynomolgus monkeys intravenously administered sibeprenlimab-szsi at doses of 25, 50, or 100 mg/kg once every two weeks for 26 weeks, no sibeprenlimab-related adverse effects on female menstrual cycle frequency and lengths, male sperm analysis of motility, concentration and count, or male and female reproductive organs were observed at doses up to 100 mg/kg, which provides an approximately 13-fold exposure margin to the clinical exposure at the MRHD based on AUC.

14 CLINICAL STUDIES

The effect of VOYXACT on proteinuria was evaluated in a randomized, double-blind, placebo-controlled, multicenter, global study (VISIONARY, NCT05248646) in adults with biopsy-confirmed IgAN, an eGFR ≥30 mL/min/1.73 m^2, proteinuria (defined as either urine protein/creatinine ratio based on 24-hour urine collections [uPCR-24h] ≥0.75 g/g or urine protein ≥1.0 g/day), and on a stable and maximally tolerated dose of an angiotensin-converting enzyme inhibitor (ACEi) and/or angiotensin receptor blocker (ARB) with or without a sodium-glucose co-transporter 2 inhibitor (SGLT2i). Patients with other glomerulopathies or those who had been treated with systemic immunosuppressants in the 16 weeks prior to screening were excluded. Patients were randomized 1:1 to receive either VOYXACT or placebo injected subcutaneously once every 4 weeks.

The study enrolled a total of 510 patients. An interim analysis for efficacy was conducted on the first 320 (63%) randomized patients who had the opportunity to reach the Month 9 visit, 152 of whom were randomized to receive VOYXACT while 168 were randomized to receive placebo. Baseline demographics and disease characteristics were generally balanced between treatment groups. At baseline, the median age was 42 years (range 18 to 83 years); 63% were male, 59% were Asian, 38% were White, and 3% were of Other race.

At baseline, mean uPCR-24h was 1.5 g/g, mean estimated glomerular filtration rate (eGFR) was 63 mL/min/1.73 m^2, and 74% had hematuria (based on urine dipstick). Approximately 67% of patients had a history of hypertension and 7% had a history of type 2 diabetes mellitus. At baseline, 98% were treated with an ACEi and/or ARB and 40% of patients were also on an SGLT2i.

The primary endpoint was the relative change from baseline in uPCR-24h at Month 9. The mean estimated percent change from baseline in uPCR-24h is shown in Figure 1. The observed geometric mean percent change from baseline over time for uPCR from spot first morning void samples is shown in Figure 2.

Figure 1: Estimated Percent Change Compared to Baseline in uPCR-24h at Month 9 in Patients with IgAN in the VISIONARY Study

VOYXACT

-50%

Placebo

2%

VOYXACT vs. Placebo (96.5% CI) [96.5% CI corresponds to the two-sided significance level of 0.035 for the interim analysis (IA).]

51% (43%, 58%)

p-value

<0.0001

CI = Confidence Interval

24-hour uPCR at Month 9 compared to baseline is defined as uPCR-24h9months/uPCR-24hBaseline.

The bar indicates the geometric mean percentage change at 9 months compared with baseline, and the whiskers indicate the 95% CI.

Data were included in the analysis regardless of early treatment discontinuation and initiation of confounding therapy (treatment policy strategy). Missing data were imputed using multiple imputation.

Figure 2: Percent Change Compared to Baseline in Spot uPCR Over Time in Patients with IgAN in the VISIONARY Study

CI = Confidence Interval

Spot uPCR at specific week is defined as spot uPCR/spot uPCRbaseline

The dots indicate the geometric mean percentage change at specific weeks compared with baseline and the whiskers indicate the corresponding 95% CIs based on observed and non-imputed spot uPCR.

The treatment effect (percentage reduction in uPCR-24h between VOYXACT and placebo) was consistent across the following subgroups and pre-specified stratification factors: sex, age, race, ethnicity, and geographic region, baseline proteinuria (uPCR-24h), baseline eGFR, and SGLT2i use.

16 HOW SUPPLIED/STORAGE AND HANDLING

How Supplied

VOYXACT (sibeprenlimab-szsi) injection is supplied as a sterile, preservative-free, clear to opalescent, colorless to yellow solution in a single-dose prefilled syringe with a 27 gauge, ½ inch needle and a needle safety device.

VOYXACT prefilled syringe is not made with natural rubber latex.

VOYXACT 400 mg/2mL (200 mg/mL) prefilled syringe is packaged in an individual carton (NDC 59148-400-75).

Storage and Handling

Store VOYXACT in a refrigerator at 36°F to 46°F (2°C to 8°C). Keep the prefilled syringe in its original box to protect it from light.

Do not freeze. Do not shake. Do not expose to heat or direct sunlight.

Once VOYXACT prefilled syringe has reached room temperature, do not return it to the refrigerator.

Do not use VOYXACT if it has been at room temperature for 7 days or longer.

17 PATIENT COUNSELING INFORMATION

Advise the patient and/or caregiver to read the FDA-approved patient labeling (Patient Information and Instructions for Use).

Infections

Inform patients that they may be more likely to develop infections when taking VOYXACT. Instruct patients to tell their healthcare provider if they develop signs or symptoms of an infection [see Warnings and Precautions (5.1)].

Hypersensitivity

Inform patients about the signs and symptoms of hypersensitivity reactions. Advise patients to discontinue VOYXACT and seek immediate medical attention for signs or symptoms of hypersensitivity reactions [see Contraindications (4)].

Pregnancy

Advise patients who are exposed to VOYXACT during pregnancy to contact Otsuka Pharmaceutical Development and Commercialization, Inc. at 1-833-869-9228 or www.VOYXACT.com.

Manufactured by:
Otsuka Pharmaceutical Company, Ltd., Tokyo, 101-8535 Japan

U.S. License No 2387

Distributed by:
Otsuka America Pharmaceutical, Inc.
Rockville, MD 20850, USA

©2025, Otsuka Pharmaceutical Co., Ltd., Tokyo, 101-8535 Japan

PATIENT INFORMATION
VOYXACT® (VOY-ZAKT)
(sibeprenlimab-szsi)
injection, for subcutaneous use

What is VOYXACT?
VOYXACT is a prescription medicine used to reduce protein in the urine (proteinuria) in adults with a kidney disease called primary immunoglobulin A nephropathy (IgAN) who are at risk for their disease getting worse.
It is not known if VOYXACT is safe and effective in children.

Do not take VOYXACT if you:

- are allergic to any of the ingredients in VOYXACT. See the end of this Patient Information for a complete list of ingredients in VOYXACT. Stop using VOYXACT and get emergency help if you develop signs and symptoms of an allergic reaction, including:

- breathing problems
- swelling of the face, lips, mouth, tongue or throat
- dizziness or feel lightheaded

- itching
- hives
- skin rash

Before taking VOYXACT, tell your healthcare provider about all of your medical conditions, including if you:

- have an infection.
- have received or plan to receive therapy that can lower the ability of your immune system to fight infections (immunosuppressive therapy).
- have recently received or are scheduled to receive an immunization (vaccine). VOYXACT may affect your immune system response to vaccines and increase your risk of infection from live vaccines.
- are pregnant or plan to become pregnant. It is not known if VOYXACT will harm your unborn baby.
- are breastfeeding or plan to breastfeed. It is not known if VOYXACT passes into your breast milk or if it will affect your baby. Talk to your healthcare provider about the best way to feed your baby during treatment with VOYXACT.

Tell your healthcare provider about all the medicines you take, including prescription and over-the-counter medicines, vitamins, and herbal supplements.

How should I take VOYXACT?

- Read the detailed "Instructions for Use" that comes with VOYXACT for information about how to prepare and inject VOYXACT, and how to properly store and throw away (dispose of) used VOYXACT prefilled syringes.
- Use VOYXACT exactly as your healthcare provider tells you to.
- VOYXACT is given as an injection under the skin (subcutaneous injection).
- Inject VOYXACT under the skin (subcutaneous injection) in the front of your upper legs (thighs) or stomach area (abdomen), avoiding the area 2 inches around the belly button. The back of the upper arms may also be used if a caregiver gives the injection.
- If you miss a dose of VOYXACT, inject the missed dose as soon as possible. Then take your next dose in 4 weeks.

What are the possible side effects of VOYXACT?
VOYXACT can cause serious side effects, including:

- immunosuppression and increased risk of infections. VOYXACT weakens your immune system, which may increase your risk of infections. Your healthcare provider will check you for signs and symptoms of infections before you start and during treatment with VOYXACT. Tell your healthcare provider right away if you develop any signs and symptoms of infection during treatment with VOYXACT, including:

- fever
- chills
- feeling tired
- cough

- flu-like symptoms
- aches and pain
- warm, red, or painful skin

The most common side effects of VOYXACT include: upper respiratory tract infection and skin redness at your injection site.
These are not all of the possible side effects of VOYXACT.
Call your doctor for medical advice about side effects. You may report side effects to FDA at 1-800-FDA-1088.

How should I store VOYXACT?

- Store VOYXACT in the refrigerator between 36°F to 46°F (2°C to 8°C).
- Keep the VOYXACT prefilled syringe in its original box to protect it from light.
- Let the VOYXACT prefilled syringe come to room temperature up to 77°F (25°C) for 15 to 30 minutes before giving the injection.
- When the VOYXACT prefilled syringe has reached room temperature, do not put it back in the refrigerator.
- Do not use VOYXACT if it has been at room temperature for 7 days or longer.
- Do not freeze the VOYXACT prefilled syringe.
- Do not shake the VOYXACT prefilled syringe.
- Keep the VOYXACT prefilled syringe away from heat and direct sunlight.
- Do not use past the expiration date printed on the box.

Keep VOYXACT and all medicines out of the reach of children.

General information about the safe and effective use of VOYXACT.
Medicines are sometimes prescribed for purposes other than those listed in a Patient Information leaflet. Do not use VOYXACT for a condition for which it was not prescribed. Do not give VOYXACT to other people, even if they have the same symptoms that you have. It may harm them. You can ask your pharmacist or healthcare provider for information about VOYXACT that is written for healthcare professionals.

What are the ingredients in VOYXACT?
Active ingredient: sibeprenlimab-szsi
Inactive ingredients: arginine, glutamic acid, histidine, L-histidine hydrochloride monohydrate, polysorbate 80, sorbitol, and Water for Injection.
VOYXACT prefilled syringe is not made with natural rubber latex.
Manufactured by:
Otsuka Pharmaceutical Company, Ltd., Tokyo, 101-8535 Japan
U.S. License No 2387
Distributed by:
Otsuka America Pharmaceutical, Inc.
Rockville, MD 20850, USA
For more information, call 1-833-869-9228 or visit www.VOYXACT.com.

This Patient Information has been approved by the U.S. Food and Drug Administration.

Issued: 11/2025

INSTRUCTIONS FOR USE

VOYXACT® (VOY-ZAKT)
(sibeprenlimab-szsi)
injection, for subcutaneous use
Single-Dose Prefilled Syringe

This Instructions for Use contains information on how to inject VOYXACT. Read and follow this Instructions for Use before you inject VOYXACT prefilled syringe for the first time and each time you get a refill. This information does not take the place of talking to your healthcare provider about your medical condition or treatment. Your healthcare provider should show you or your caregiver how to prepare and inject VOYXACT the right way before you use or give it for the first time.

Important Information You Need to Know Before Injecting VOYXACT Prefilled Syringe

- VOYXACT prefilled syringe is for injection under the skin (subcutaneous injection) use only.
- Do not remove the grey needle cap from the prefilled syringe until you are ready to inject.
- Each prefilled syringe has a needle guard. It will automatically cover the needle after the injection is completed.
- Do not pull back on the plunger at any time.
- Do not use if the VOYXACT prefilled syringe has been damaged.
- Do not use if the VOYXACT prefilled syringe has been dropped after removing the needle cap.

Storing VOYXACT Prefilled Syringe

- Store your VOYXACT prefilled syringe in a refrigerator between 36°F to 46°F (2°C to 8°C). Keep the prefilled syringe in its original box to protect it from light.
- Let the VOYXACT prefilled syringe come to room temperature up to 77°F (25°C) for 15 to 30 minutes before giving an injection.
- When the VOYXACT prefilled syringe has reached room temperature, do not put it back in the refrigerator.
- Do not use the VOYXACT prefilled syringe if it has been at room temperature for 7 days or longer.
- Do not freeze the VOYXACT prefilled syringe.
- Do not shake the VOYXACT prefilled syringe.
- Keep the VOYXACT prefilled syringe away from heat and direct sunlight.
- Throw away (dispose of) any VOYXACT prefilled syringe if it is expired. See Step 11 for instructions on how to throw away (dispose of) the VOYXACT prefilled syringe.
- Keep VOYXACT prefilled syringe and all medicines out of the reach of children.

Your VOYXACT Single-Dose Prefilled Syringe

Getting Your Supplies Ready

Step 1: Remove the VOYXACT prefilled syringe box from the refrigerator

Take the box containing VOYXACT prefilled syringe out of the refrigerator and check the expiration date (EXP) on the side of the box.

- Do not use the prefilled syringe if the seals on the box have been broken.
- Do not use the prefilled syringe if the expiration date (EXP) printed on the box has passed.

Step 2: Wait 15 to 30 minutes before use

Wait 15 to 30 minutes to let the prefilled syringe come to room temperature naturally (see Figure A).

- Do not warm the prefilled syringe any other way.
- Do not let the prefilled syringe sit in direct sunlight.

Figure A

Step 3: Gather supplies

Gather supplies that are not included in the VOYXACT prefilled syringe box:

- Alcohol swabs
- Cotton balls or gauze
- Adhesive bandages
- Sharps disposal container (see Step 11)

Preparing to Inject the VOYXACT Prefilled Syringe

Step 4: Take the VOYXACT prefilled syringe out of the box

Hold the middle of the prefilled syringe (near the viewing window) to carefully lift the prefilled syringe out of the box (see Figure B).

- Do not lift the prefilled syringe by the plunger.
- Do not shake or roll the prefilled syringe.
- Do not remove the grey needle cap from the prefilled syringe until Step 8 and you are ready to inject.

Figure B

Step 5: Inspect the VOYXACT Prefilled Syringe

- Make sure that VOYXACT appears on the labels.
- Check the expiration date (EXP) printed on the prefilled syringe (see Figure C).
- Check the medicine in the prefilled syringe through the viewing window. It is normal to see air bubbles. The medicine inside should be clear to slightly pearly and colorless to yellow (see Figure C).
- Do not use VOYXACT prefilled syringe if:
  - the expiration date printed on the prefilled syringe label has passed.
  - the medicine is cloudy, discolored, or has particles floating in it.
  - any part of the prefilled syringe is damaged, broken, or the needle guard has been activated.
- Do not try to remove air bubble(s) from the prefilled syringe.

Figure C

Step 6: Choose the injection site

Choose an injection site on your bare skin from 1 of the following areas (see Figure D):

- front of upper thigh
- stomach area (abdomen), avoiding the area 2 inches around the belly button.
  For caregiver only: back of the upper arm may also be used.
- Do not inject into the same spot you used for your last injection.
- Do not inject into moles, scars, or bruises or skin that is tender, damaged, hard or red.

Figure D

Step 7: Clean the injection site

Wash your hands with soap and clean water (see Figure E).

Figure E

- Clean the injection site with an alcohol swab and let the skin dry (see Figure F).
- Do not touch the area again before injecting.
- Do not fan or blow on the injection site after you have cleaned it.

Figure F

Injecting VOYXACT

Step 8: Remove the needle cap

When you are ready to inject, hold the prefilled syringe with 1 hand, pull the needle cap straight off with the other hand (see Figure G).

- You may see a drop of liquid at the end of the needle. This is normal.
- Do not touch or recap the needle or let it touch any surface.
- Do not touch or pull back the plunger.
- Do not use a prefilled syringe with a bent or broken needle.

Figure G

Step 9: Pinch the skin and insert needle

With the needle cap off, hold the prefilled syringe in 1 hand. With your other hand, gently pinch the skin at the injection site (see Figure H).

- It is important to pinch enough skin to inject under the skin and not into the muscle.

Insert the entire needle at a 45-degree angle into the pinched skin using a dart-like motion (see Figure H).

- Avoid touching the plunger until the needle is inserted.

Figure H

Step 10: Complete the Injection

Push the plunger as far as it will go and it stops, and all the medicine is injected (see Figure I).

Figure I

Take your thumb off the plunger to allow the needle guard to automatically cover the exposed needle (see Figure J).

Figure J

Gently lift the syringe away from the injection site (see Figure K).

- There may be a small amount of blood or liquid at the injection site. Hold pressure over your skin with a cotton ball or gauze until any bleeding stops.
- Apply an adhesive bandage, if needed.
- Do not rub or massage the injection site.

Figure K

Disposing of the VOYXACT Prefilled Syringe

Step 11: Throw away (dispose of) the VOYXACT prefilled syringe

Throw away (dispose of) the used prefilled syringe in a FDA-cleared sharps disposal container right away after use (see Figure L). Do not recycle or throw away the prefilled syringe in your household trash.

Figure L

- Throw away the remaining supplies in your household trash or sharps container.
- If you do not have a FDA-cleared sharps disposal container, you may use a household container that is:

- made of a heavy-duty plastic,
- can be closed with a tight-fitting, puncture-resistant lid, without sharps being able to come out,
- upright and stable during use,
- leak-resistant, and
- properly labeled to warn of hazardous waste inside the container.

- When your sharps disposal container is almost full, you will need to follow your community guidelines for the right way to dispose of your sharps disposal container. There may be local or state laws about how to throw away needles and syringes.
- For more information about safe sharps disposal, and for specific information about sharps disposal in the state that you live in, go to the FDA's website at: http://www.fda.gov/safesharpsdisposal.
- Do not recycle your used sharps disposal container.

If you have questions or concerns about your VOYXACT prefilled syringe, please call your healthcare provider. You can also call 1-800-441-6763 or visit www.VOYXACT.com for more information.

Manufactured by:
Otsuka Pharmaceutical Company, Ltd.

Tokyo 101-8535 Japan
U.S. License No 2387

Distributed by:
Otsuka America Pharmaceutical, Inc.
Rockville, MD 20850 USA

This Instructions for Use has been approved by the U.S. Food and Drug Administration. | Issued: Nov 2025

PRINCIPAL DISPLAY PANEL - 200 mg/mL Syringe Carton

NDC 59148-400-75

Rx only

Voyxact®
(sibeprenlimab-szsi)
Injection

400 mg/2 mL
(200 mg/mL)

For Subcutaneous Use Only

Contains one single-dose prefilled syringe.
Discard after use.